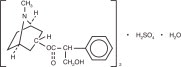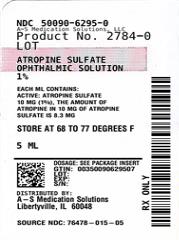 DRUG LABEL: Atropine
NDC: 50090-6295 | Form: SOLUTION/ DROPS
Manufacturer: A-S Medication Solutions
Category: prescription | Type: HUMAN PRESCRIPTION DRUG LABEL
Date: 20221227

ACTIVE INGREDIENTS: ATROPINE SULFATE 10 mg/1 mL
INACTIVE INGREDIENTS: Benzalkonium Chloride; Sodium Phosphate, Dibasic, Unspecified Form; Edetate Disodium; Hypromellose 2910 (4000 MPA.S); Sodium Phosphate, Monobasic, Unspecified Form; Hydrochloric Acid; Sodium Hydroxide; Water

HIGHLIGHTS OF PRESCRIBING INFORMATION

These highlights do not include all the information needed to use Atropine Sulfate Ophthalmic Solution, USP 1% safely and effectively. See full prescribing information for Atropine Sulfate Ophthalmic Solution, USP 1%.
Atropine Sulfate Ophthalmic Solution, USP 1% for topical application to the eye.
Initial U.S. Approval: 1960

1. INDICATIONS AND USAGE

Atropine is an anti-muscarinic agent indicated for:

- Cycloplegia (1.1)
- Mydriasis (1.2)
- Penalization of the healthy eye in the treatment of amblyopia (1.3)

2. DOSAGE AND ADMINISTRATION

- In individuals from three (3) months of age or greater, 1 drop topically to the cul-de-sac of the conjunctiva, forty minutes prior to the intended maximal dilation time. (2)
- In individuals 3 years of age or greater, doses may be repeated up to twice daily as needed. (2)

3. DOSAGE FORMS AND STRENGTHS

1% ophthalmic solution (3)

4. CONTRAINDICATIONS

Hypersensitivity or allergic reaction to any ingredient in formulation. (4.1)

5. WARNINGS AND PRECAUTIONS

- Photophobia and blurred vision due to pupil unresponsiveness and cycloplegia may last up to 2 weeks. (5.1)
- Risk of blood pressure increase from systemic absorption. (5.2)

6. ADVERSE REACTIONS

Most common adverse reactions that have been reported are eye pain and stinging on administration, blurred vision, photophobia, decreased lacrimation, increased heart rate and blood pressure. (6)

To report SUSPECTED ADVERSE REACTIONS, contact, Akorn Operating Company LLC at 1-800-932-5676 or FDA at 1-800-FDA-1088 or www.fda.gov/medwatch

7. DRUG INTERACTIONS

The use of atropine and monoamine oxidase inhibitors (MAOI) is generally not recommended because of the potential to precipitate hypertensive crisis. (7)

8. USE IN SPECIFIC POPULATIONS

Should only be used in pregnant women if clearly needed. (8)

FULL PRESCRIBING INFORMATION

1. INDICATIONS AND USAGE

Atropine Sulfate Ophthalmic Solution, USP 1% is indicated for:

2. DOSAGE AND ADMINISTRATION

- In individuals from three (3) months of age or greater, 1 drop topically to the cul-de-sac of the conjunctiva, forty minutes prior to the intended maximal dilation time.
- In individuals 3 years of age or greater, doses may be repeated up to twice daily as needed.

3. DOSAGE FORMS AND STRENGTHS

Atropine Sulfate Ophthalmic Solution, USP 1%: each mL contains 10 mg of atropine sulfate equivalent to 8.3 mg of atropine.

4. CONTRAINDICATIONS

4.1 Hypersensitivity to any Component of this Medication

Atropine sulfate ophthalmic solution should not be used in anyone who has demonstrated a previous hypersensitivity or known allergic reaction to any ingredient of the formulation because it may recur.

5. WARNINGS AND PRECAUTIONS

5.1 Photophobia and Blurred Vision

Photophobia and blurred vision due to pupil unresponsiveness and cycloplegia may last up to 2 weeks.

5.2 Elevation of Blood Pressure

Elevations in blood pressure from systemic absorption has been reported following conjunctival instillation of recommended doses of atropine sulfate ophthalmic solution, USP 1%.

6. ADVERSE REACTIONS

The following serious adverse reactions are described below and elsewhere in the labeling:

- Photophobia and Blurred Vision [See Warnings and Precautions (5.1)]
- Elevation in Blood Pressure [See Warnings and Precautions (5.2)]

The following adverse reactions have been identified following use of atropine sulfate ophthalmic solution. Because these reactions are reported voluntarily from a population of uncertain size, it is not always possible to reliably estimate their frequency or establish a causal relationship to drug exposure.

6.1 Ocular Adverse Reactions

Eye pain and stinging occurs upon instillation of atropine sulfate ophthalmic solution. Other commonly occurring adverse reactions include, blurred vision, photophobia, superficial keratitis and decreased lacrimation. Allergic reactions such as papillary conjunctivitis, contact dermatitis, and lid edema may also occur less commonly.

6.2 Systemic Adverse Reactions

Systemic effects of atropine are related to its anti-muscarinic activity. Systemic adverse events reported include dryness of skin, mouth, and throat from decreased secretions from mucus membranes; restlessness, irritability or delirium from stimulation of the central nervous system; tachycardia; flushed skin of the face and neck.

7. DRUG INTERACTIONS

7.1 Monoamine oxidase inhibitors (MAOI)

The use of atropine and monoamine oxidase inhibitors (MAOI) is generally not recommended because of the potential to precipitate hypertensive crisis.

8. USE IN SPECIFIC POPULATIONS

8.1 Pregnancy

Pregnancy Category C:

There are no adequate and well-controlled studies of atropine sulfate in pregnant women. Animal development and reproduction studies have not been conducted with atropine sulfate. Since it is not known whether topically administered atropine sulfate can cause fetal harm, atropine sulfate ophthalmic solution, USP 1% should only be used during pregnancy if the potential benefit justifies the potential risk to the fetus.

8.3 Nursing Mothers

Traces of atropine have been found in human milk following administration of atropine solution for injection. Because some systemic absorption occurs from topical administration, caution should be exercised when Atropine Sulfate Ophthalmic Solution, USP 1% is administered to a nursing woman.

8.4 Pediatric Use

Due to the potential for systemic absorption of atropine sulfate ophthalmic solution, the use of atropine sulfate ophthalmic solution, USP 1% in children under the age of 3 months is not recommended and the use in children under 3 years of age should be limited to no more than one drop per eye per day.

8.5 Geriatric Use

No overall differences in safety and effectiveness have been observed between elderly and younger adult patients.

10. OVERDOSAGE

In the event of accidental ingestion or toxic overdosage with atropine sulfate ophthalmic solution, supportive care may include a short acting barbiturate or diazepam as needed to control marked excitement and convulsions. Large doses for sedation should be avoided because central depressant action may coincide with the depression occurring late in atropine poisoning. Central stimulants are not recommended.

Physostigmine, given by slow intravenous injection of 1 to 4 mg (0.5 to 1 mg in pediatric populations), rapidly abolishes delirium and coma caused by large doses of atropine. Since physostigmine is rapidly destroyed, the patient may again lapse into coma after one to two hours, and repeated doses may be required.

Artificial respiration with oxygen may be necessary. Cooling measures may be needed to help to reduce fever, especially in pediatric populations.

The fatal adult dose of atropine is not known. In pediatric populations, 10 mg or less maybe fatal.

11. DESCRIPTION

Atropine Sulfate Ophthalmic Solution, USP 1% is a sterile topical anticholinergic for ophthalmic use. The active ingredient is represented by the chemical structure:

Chemical Name: Benzeneacetic acid, α-(hydroxymethyl)-, 8-methyl- 8-azabicyclo[3.2.1.]oct-3-yl ester, endo -(±)-, sulfate (2:1) (salt), monohydrate.

Molecular Formula: (C17H23NO3)2 • H2SO4 • H2O

Molecular Weight: 694.83 g/mol

Each mL of Atropine Sulfate Ophthalmic Solution USP, 1% contains:

Active: atropine sulfate 10 mg equivalent to 8.3 mg of atropine.

Inactives: benzalkonium chloride 0.1 mg (0.01%), dibasic sodium phosphate, edetate disodium, hypromellose (2910), monobasic sodium phosphate, hydrochloric acid and/or sodium hydroxide may be added to adjust pH (3.5 to 6.0), and water for injection USP.

12. CLINICAL PHARMACOLOGY

12.1 Mechanism of Action

Atropine is a reversible antagonist of muscarine-like actions of acetyl-choline and is therefore classified as an antimuscarinic agent. Atropine is relatively selective for muscarinic receptors. Its potency at nicotinic receptors is much lower, and actions at non-muscarinic receptors are generally undetectable clinically. Atropine does not distinguish among the M1, M2, and M3 subgroups of muscarinic receptors.

The pupillary constrictor muscle depends on muscarinic cholinoceptor activation. This activation is blocked by topical atropine resulting in unopposed sympathetic dilator activity and mydriasis. Atropine also weakens the contraction of the ciliary muscle, or cycloplegia. Cycloplegia results in loss of the ability to accommodate such that the eye cannot focus for near vision.

12.2 Pharmacodynamics

The onset of action after administration of atropine sulfate ophthalmic solution, USP 1%, is usually within 40 minutes with maximal effect being reached in about 2 hours. The effect can last for up to 2 weeks in a normal eye.

12.3 Pharmacokinetics

The bioavailability of atropine sulfate ophthalmic solution, USP 1% was assessed in six healthy subjects, 24 to 29 years of age. Subjects received either 0.3 mg atropine sulfate administered as bolus intravenous injection or 0.3 mg administered as 30 μl instilled unilaterally in the cul-de-sac of the eye. Plasma l-hyoscyamine concentrations were determined over selected intervals up to eight hours after dose administration.

The mean bioavailability of topically applied atropine was 63.5 ± 29% (range 19 to 95%) with large inter-individual differences. Mean maximum observed plasma concentration for the ophthalmic solution was 288 ± 73 pg/mL. Maximum concentration was reached in 28 ± 27 min after administration. Terminal half-life of l-hyoscamine was not affected by route of administration and was calculated to be 3 ± 1.2 hours (intravenous) and 2.5 ± 0.8 hours (topical ophthalmic).

In another placebo-controlled study, the systemic exposure to 1-hyoscyamine, and the anti-cholinergic effects of atropine were investigated in eight ocular surgery patients 56 to 66 years of age, following single topical ocular 0.4 mg atropine dose (given as 40 microliters of atropine sulfate ophthalmic solution, USP 1%). The mean (± standard deviation (SD)) Cmax of l-hyoscyamine in these patients was 860 ± 402 pg/mL, achieved within 8 minutes of eyedrop instillation.

Following intravenous administration, the mean (± SD) elimination half-life (t1/2) of atropine was reported to be longer in pediatric subjects under 2 years (6.9 ± 3.3 hours) and in geriatric patients 65 to 75 years (10.0 ± 7.3 hours), compared to in children over 2 years (2.5 ± 1.2 hours) and in adults 16 to 58 years (3.0 ± 0.9 hours). (See 8.4 Pedriatic Use).

Atropine is destroyed by enzymatic hydrolysis, particularly in the liver; from 13 to 50% is excreted unchanged in the urine. Traces are found in various secretions, including milk. The major metabolites of atropine are noratropine, atropin-n-oxide, tropine, and tropic acid. Atropine readily crosses the placental barrier and enters the fetal circulation, but is not found in amniotic fluid.

Atropine binds poorly (about 44%) to plasma protein, mainly to alpha-1 acid glycoprotein; age has no effect on the serum protein binding of atropine. Atropine binding to α-1 acid glycoprotein was concentration dependent (2 to 20 mcg/mL) and nonlinear in vitro and in vivo. There is no gender effect on the pharmacokinetics of atropine administered by injection.

13. NONCLINICAL TOXICOLOGY

13.1 Carcinogenesis, Mutagenesis, Impairment of Fertility

Atropine sulfate was negative in the salmonella/microsome mutagenicity test. Studies to evaluate carcinogenicity and impairment of fertility have not been conducted.

14. CLINICAL STUDIES

Topical administration of atropine sulfate ophthalmic solution, USP 1% results in cycloplegia and mydriasis which has been demonstrated in several controlled clinical studies in adults and pediatric patients. Maximal mydriasis usually occurs in about 40 minutes and maximal cycloplegia is usually achieved in about 60 to 90 minutes after single administration. Full recovery usually occurs in approximately one week, but may last a couple of weeks.

16. HOW SUPPLIED/STORAGE AND HANDLING

Product: 50090-6295

NDC: 50090-6295-0 5 mL in a BOTTLE, DROPPER / 1 in a CARTON

17. PATIENT COUNSELING INFORMATION

Advise patients not to touch the dropper tip to any surface as this may contaminate the solution.

Advise patients that drops will sting upon instillation and advise patients that they will experience sensitivity to light and blurred vision which may last for a couple of weeks.

AKORN
Distributed by:
Akorn Operating Company LLC
Gurnee, IL 60031
OAS00N Rev. 05/22